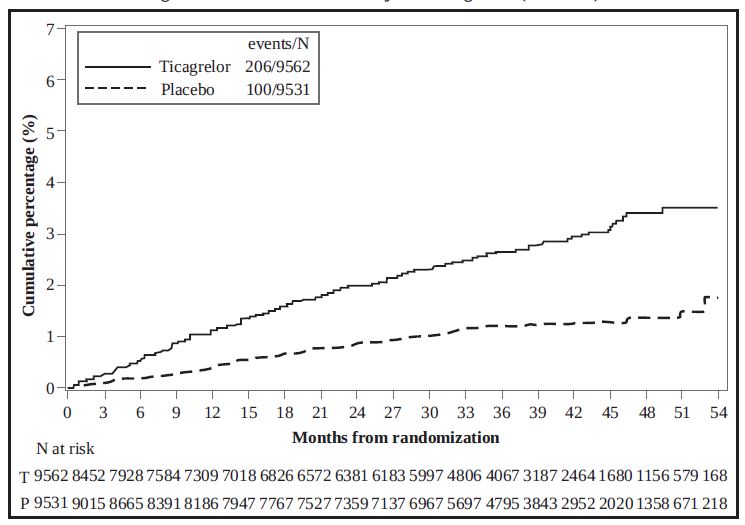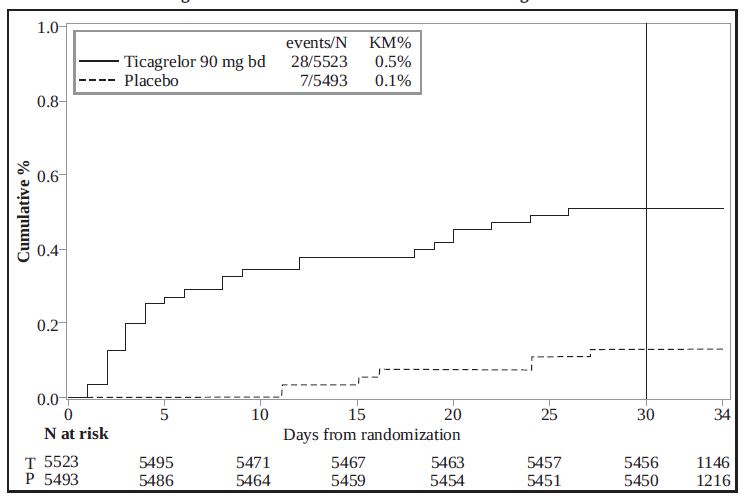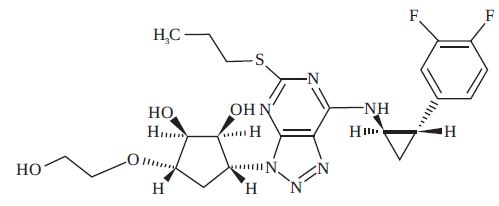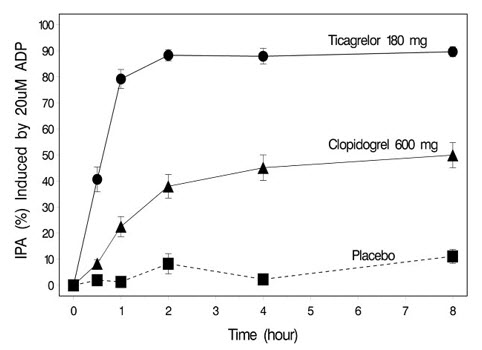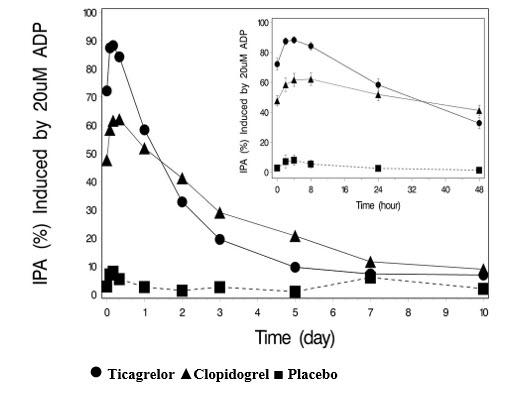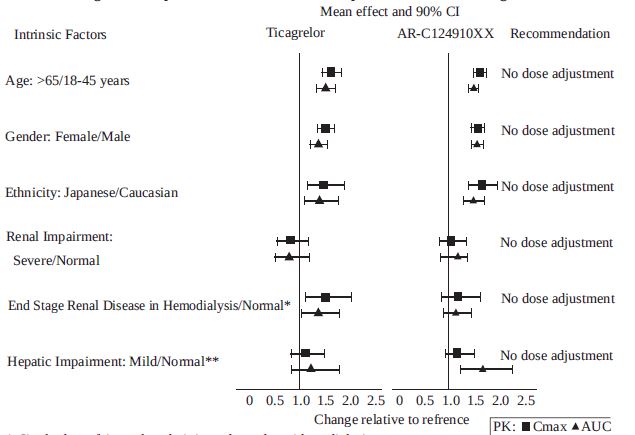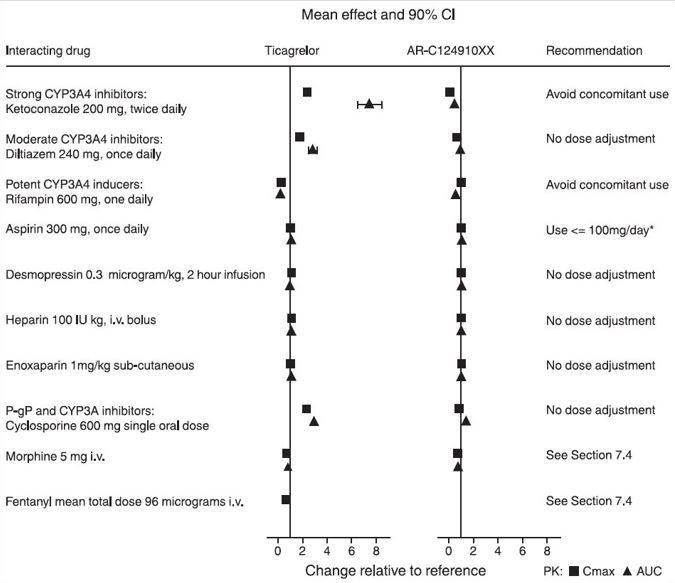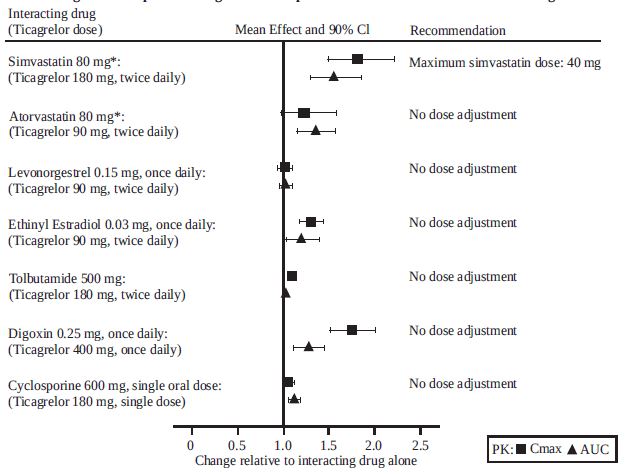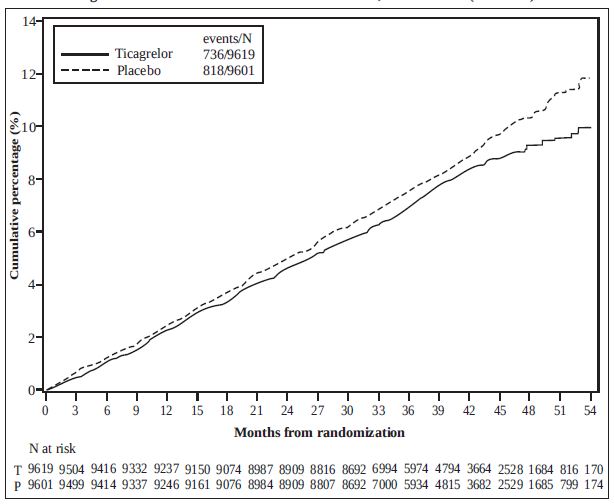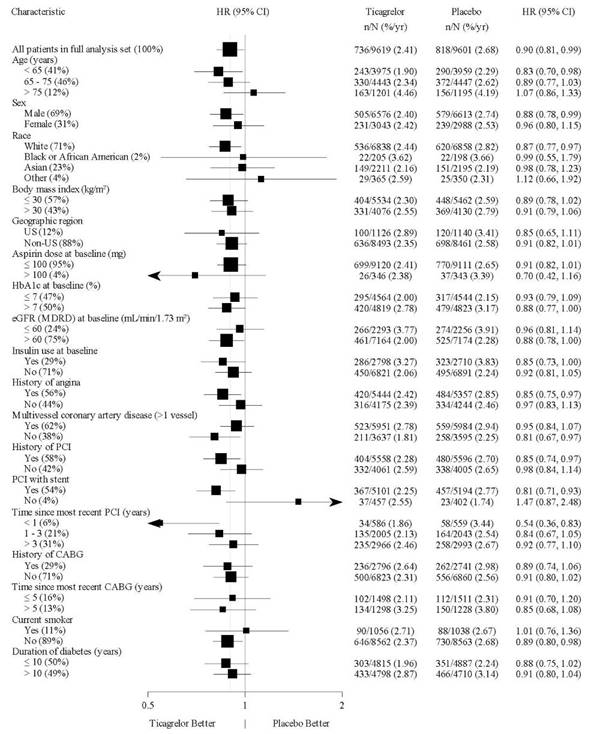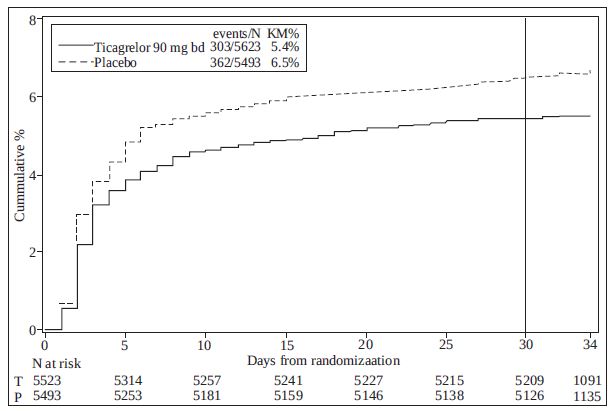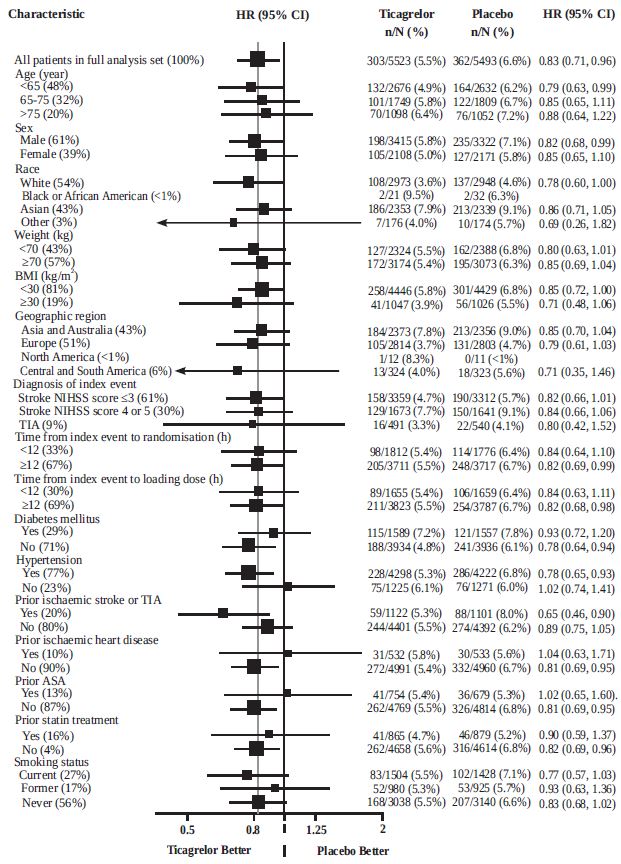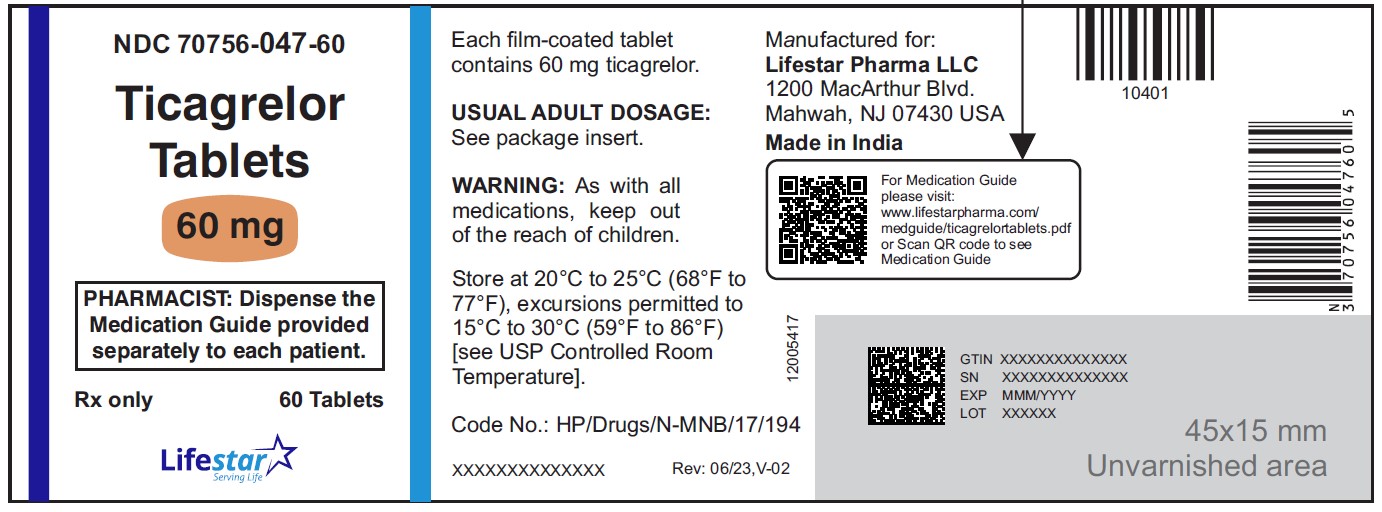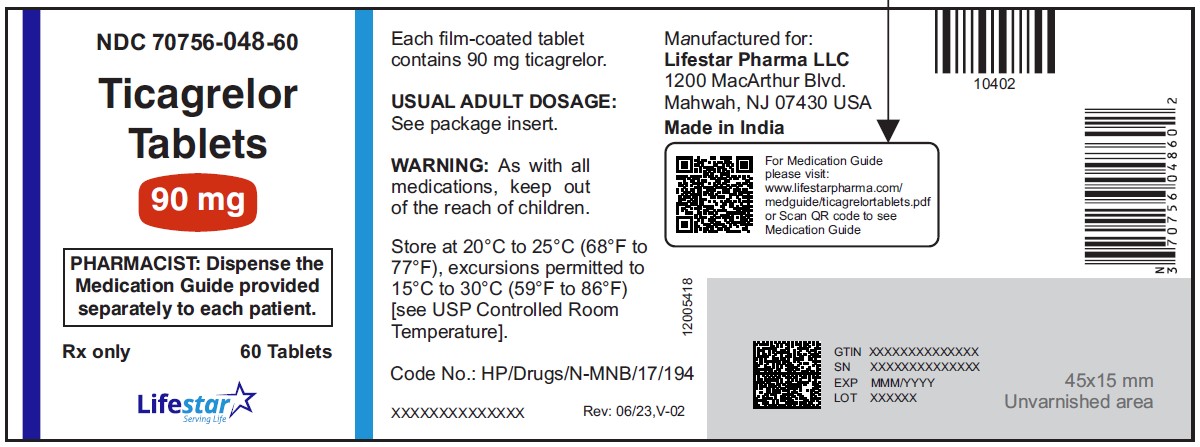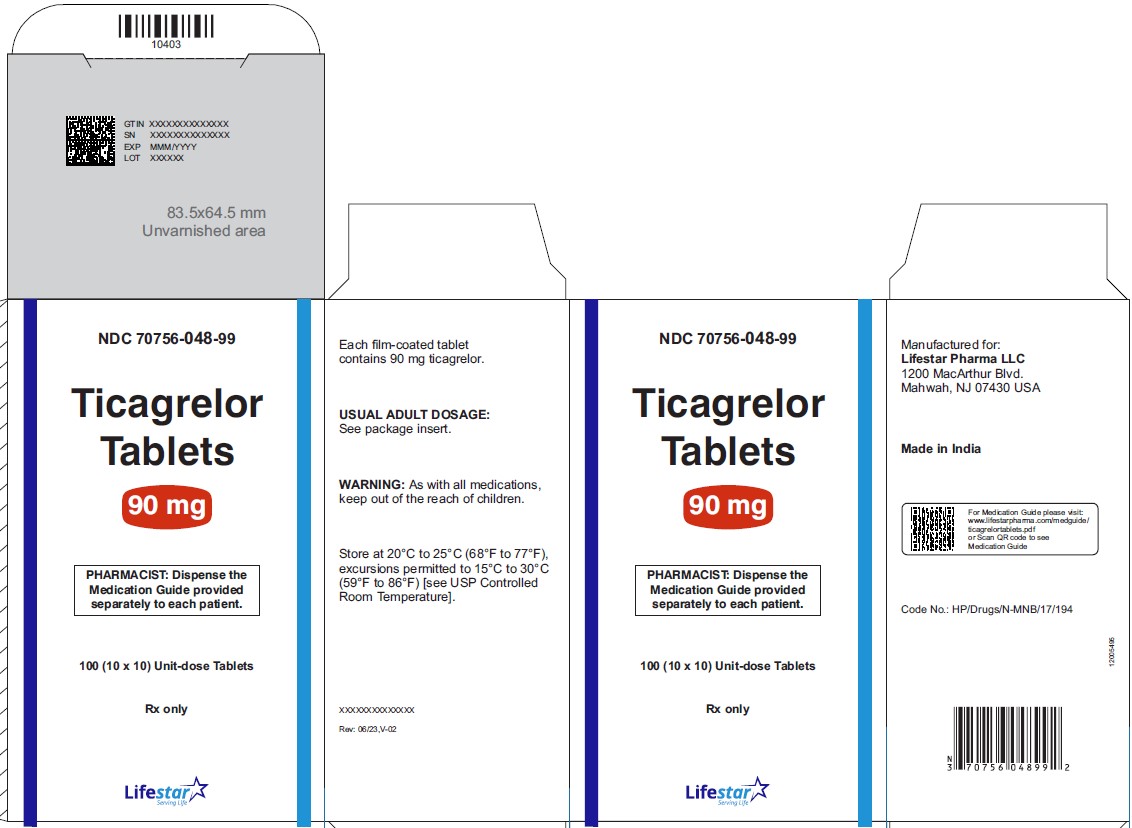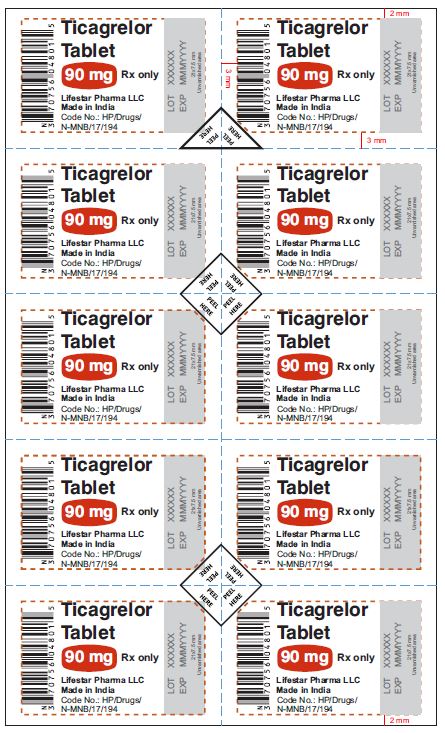 DRUG LABEL: Ticagrelor
NDC: 70756-047 | Form: TABLET, FILM COATED
Manufacturer: Lifestar Pharma LLC
Category: prescription | Type: HUMAN PRESCRIPTION DRUG LABEL
Date: 20260212

ACTIVE INGREDIENTS: TICAGRELOR 60 mg/1 1
INACTIVE INGREDIENTS: CROSCARMELLOSE SODIUM; CALCIUM PHOSPHATE, DIBASIC, DIHYDRATE; HYPROMELLOSE 2910 (6 MPA.S); MAGNESIUM STEARATE; MANNITOL; POVIDONE K30; TITANIUM DIOXIDE; D&C YELLOW NO. 10 ALUMINUM LAKE; FD&C BLUE NO. 1 ALUMINUM LAKE; FD&C RED NO. 40; POLYETHYLENE GLYCOL 400

HIGHLIGHTS OF PRESCRIBING INFORMATION

These highlights do not include all the information needed to use TICAGRELOR TABLETS safely and effectively. See full prescribing information for TICAGRELOR TABLETS.
TICAGRELOR tablets, for oral use
Initial U.S. Approval: 2011

WARNING: BLEEDING RISK

See full prescribing information for complete boxed warning.

- Ticagrelor, like other antiplatelet agents, can cause significant, sometimes fatal bleeding. (5.1, 6.1)
- Do not use ticagrelor in patients with active pathological bleeding or a history of intracranial hemorrhage. (4.1, 4.2)
- Do not start ticagrelor in patients undergoing urgent coronary artery bypass graft surgery (CABG). (5.1, 6.1)
- If possible, manage bleeding without discontinuing ticagrelor. Stopping ticagrelor increases the risk of subsequent cardiovascular events. (5.4)

RECENT MAJOR CHANGES

Dosage and Administration (2.2, 2.4) 03/2024

1 INDICATIONS AND USAGE

Ticagrelor tablets are P2Y12 platelet inhibitor indicated

- to reduce the risk of a first MI or stroke in patients with coronary artery disease (CAD) at high risk for such events. While use is not limited to this setting, the efficacy of ticagrelor tablets was established in a population with type 2 diabetes mellitus (T2DM). (1.2)
- to reduce the risk of stroke in patients with acute ischemic stroke (NIH Stroke Scale score ≤5) or high-risk transient ischemic attack (TIA). (1.3)

2 DOSAGE AND ADMINISTRATION

- Patients with CAD and No Prior Stroke or MI
- Administer 60 mg ticagrelor tablets twice daily. (2.3)
- Acute Ischemic Stroke
- Initiate treatment with a 180 mg loading dose of ticagrelor tablets then continue with 90 mg twice daily for up to 30 days. (2.3)

Use ticagrelor tablets with a daily maintenance dose of aspirin of 75-100 mg. (2)

3 DOSAGE FORMS AND STRENGTHS

- 60 mg and 90 mg tablets (3)

4 CONTRAINDICATIONS

- History of intracranial hemorrhage. (4.1)
- Active pathological bleeding. (4.2)
- Hypersensitivity to ticagrelor or any component of the product. (4.3)

5 WARNINGS AND PRECAUTIONS

- Dyspnea was reported more frequently with ticagrelor than with control agents in clinical trials. Dyspnea from ticagrelor is self-limiting. (5.3)
- Severe Hepatic Impairment: Likely increase in exposure to ticagrelor. (5.6)
- Laboratory Test Interference: False negative platelet functional test results have been reported for Heparin Induced Thrombocytopenia (HIT). Ticagrelor is not expected to impact PF4 antibody testing for HIT. (5.8)

6 ADVERSE REACTIONS

Most common adverse reactions (>5%) are bleeding and dyspnea. (5.1, 5.3, 6.1)

To report SUSPECTED ADVERSE REACTIONS, contact Lifestar Pharma LLC at 1-888-995-4337 or FDA at 1-800-FDA-1088 or www.fda.gov/medwatch.

7 DRUG INTERACTIONS

- Avoid use with strong CYP3A inhibitors or CYP3A inducers. (7.1, 7.2)
- Opioids: Decreased exposure to ticagrelor. Consider use of parenteral anti-platelet agent. (7.3)
- Patients receiving more than 40 mg per day of simvastatin or lovastatin may be at increased risk of statin-related adverse effects. (7.4)
- Rosuvastatin plasma concentrations may increase. Monitor for statin-related adverse effects. (7.4)
- Monitor digoxin levels with initiation of or any change in ticagrelor. (7.5)

8 USE IN SPECIFIC POPULATIONS

- Lactation: Breastfeeding not recommended. (8.2)

FULL PRESCRIBING INFORMATION

WARNING: BLEEDING RISK

- Ticagrelor, like other antiplatelet agents, can cause significant, sometimes fatal bleeding (5.1, 6.1).
- Do not use ticagrelor in patients with active pathological bleeding or a history of intracranial hemorrhage (4.1, 4.2).
- Do not start ticagrelor in patients undergoing urgent coronary artery bypass graft surgery (CABG) (5.1, 6.1).
- If possible, manage bleeding without discontinuing ticagrelor. Stopping ticagrelor increases the risk of subsequent cardiovascular events (5.4).

1 INDICATIONS AND USAGE

1.2 Coronary Artery Disease but No Prior Stroke or Myocardial Infarction

Ticagrelor tablets are indicated to reduce the risk of a first MI or stroke in patients with coronary artery disease (CAD) at high risk for such events [see Clinical Studies (14.2)]. While use is not limited to this setting, the efficacy of ticagrelor tablets was established in a population with type 2 diabetes mellitus (T2DM).

1.3 Acute Ischemic Stroke or Transient Ischemic Attack (TIA)

Ticagrelor tablets are indicated to reduce the risk of stroke in patients with acute ischemic stroke (NIH Stroke Scale score ≤5) or high-risk transient ischemic attack (TIA) [see Clinical Studies (14.3)].

2 DOSAGE AND ADMINISTRATION

2.1 General Instructions

Advise patients who miss a dose of ticagrelor tablets to take their next dose at its scheduled time.

For patients who are unable to swallow tablets whole, ticagrelor tablets tablets can be crushed, mixed with water, and drunk. The mixture can also be administered via a nasogastric tube (CH8 or greater) [see Clinical Pharmacology (12.3)].

Do not administer ticagrelor tablets with another oral P2Y12 platelet inhibitor.

Avoid aspirin at doses higher than recommended [see Clinical Studies (14.1)].

2.3 Coronary Artery Disease but No Prior Stroke or Myocardial Infarction

Administer 60 mg of ticagrelor tablets twice daily.

Generally, use ticagrelor tablets with a daily maintenance dose of aspirin of 75 mg to 100 mg [see Clinical Studies (14)].

2.4 Acute Ischemic Stroke or Transient Ischemic Attack (TIA)

Initiate treatment with a 180 mg loading dose of ticagrelor tablets and then continue with 90 mg twice daily for up to 30 days. Administer the first maintenance dose 6 to 12 hours after the loading dose. (14.3)].

Use ticagrelor tablets with a loading dose of aspirin (300 mg to 325 mg) and a daily maintenance dose of aspirin of 75 mg to 100 mg [see Clinical Studies (14)].

3 DOSAGE FORMS AND STRENGTHS

Ticagrelor tablets 60 mg are supplied as light green to green colored, round, biconvex, film-coated tablets, debossed with 'L47' on one side and plain on other side.

Ticagrelor tablets 90 mg are supplied as white to off white, round, biconvex, film- coated tablets, debossed with 'L48' on one side and plain on other side.

4 CONTRAINDICATIONS

4.1 History of Intracranial Hemorrhage

Ticagrelor tablets are contraindicated in patients with a history of intracranial hemorrhage (ICH) because of a high risk of recurrent ICH in this population [see Clinical Studies (14.2)].

4.2 Active Bleeding

Ticagrelor tablets are contraindicated in patients with active pathological bleeding such as peptic ulcer or intracranial hemorrhage [see Warnings and Precautions (5.1) and Adverse Reactions (6.1)].

4.3 Hypersensitivity

Ticagrelor tablets are contraindicated in patients with hypersensitivity (e.g., angioedema) to ticagrelor or any component of the product.

5 WARNINGS AND PRECAUTIONS

5.1 Risk of Bleeding

Drugs that inhibit platelet function including ticagrelor increase the risk of bleeding [see Warnings and Precautions (5.2) and Adverse Reactions (6.1)].

Patients treated for acute ischemic stroke or TIA

Patients at NIHSS >5 and patients receiving thrombolysis were excluded from THALES and use of ticagrelor in such patients is not recommended.

5.2 Discontinuation of Ticagrelor in Patients Treated for Coronary Artery Disease

Discontinuation of ticagrelor will increase the risk of myocardial infarction, stroke, and death in patients being treated for coronary artery disease. If ticagrelor must be temporarily discontinued (e.g., to treat bleeding or for significant surgery), restart it as soon as possible. When possible, interrupt therapy with ticagrelor for five days prior to surgery that has a major risk of bleeding. Resume ticagrelor as soon as hemostasis is achieved.

5.3 Dyspnea

In clinical trials, about 21% (THEMIS) of patients treated with ticagrelor developed dyspnea. Dyspnea was usually mild to moderate in intensity and often resolved during continued treatment but led to study drug discontinuation in 1.0% (THALES) and 6.9% (THEMIS) of patients.

If a patient develops new, prolonged, or worsened dyspnea that is determined to be related to ticagrelor, no specific treatment is required; continue ticagrelor without interruption if possible. In the case of intolerable dyspnea requiring discontinuation of ticagrelor, consider prescribing another antiplatelet agent.

5.4 Bradyarrhythmias

Ticagrelor can cause ventricular pauses [see Adverse Reactions (6.1)]. Bradyarrhythmias including AV block have been reported in the postmarketing setting. Patients with a history of sick sinus syndrome, 2nd or 3rd degree AV block or bradycardia-related syncope not protected by a pacemaker were excluded from clinical studies and may be at increased risk of developing bradyarrhythmias with ticagrelor.

5.5 Severe Hepatic Impairment

Avoid use of ticagrelor in patients with severe hepatic impairment. Severe hepatic impairment is likely to increase serum concentration of ticagrelor. There are no studies of ticagrelor patients with severe hepatic impairment [see Clinical Pharmacology (12.3)].

5.6 Central Sleep Apnea

Central sleep apnea (CSA) including Cheyne-Stokes respiration (CSR) has been reported in the post-marketing setting in patients taking ticagrelor, including recurrence or worsening of CSA/CSR following rechallenge. If central sleep apnea is suspected, consider further clinical assessment.

5.7 Laboratory Test Interferences

False negative functional tests for Heparin Induced Thrombocytopenia (HIT)

Ticagrelor has been reported to cause false negative results in platelet functional tests (including, the heparin-induced platelet aggregation (HIPA) assay) for patients with Heparin Induced Thrombocytopenia (HIT). This is related to inhibition of the P2Y12-receptor on the healthy donor platelets in the test by ticagrelor in the affected patient's serum/plasma. Information on concomitant treatment with ticagrelor is required for interpretation of HIT functional tests. Based on the mechanism of ticagrelor interference, ticagrelor is not expected to impact PF4 antibody testing for HIT.

6 ADVERSE REACTIONS

The following adverse reactions are also discussed elsewhere in the labeling:

- Bleeding [see Warnings and Precautions (5.1)]
- Dyspnea [see Warnings and Precautions (5.3)]

6.1 Clinical Trials Experience

Because clinical trials are conducted under widely varying conditions, adverse reaction rates observed in the clinical trials of a drug cannot be directly compared to rates in the clinical trials of another drug and may not reflect the rates observed in practice.

Ticagrelor has been evaluated for safety in more than 58,000 patients.

Bleeding in THEMIS (Prevention of major CV events in patients with CAD and Type 2 Diabetes Mellitus)

The Kaplan-Meier curve of time to first TIMI Major bleeding event is presented in Figure 3.

Figure 3 - Time to first TIMI Major bleeding event (THEMIS)

T = Ticagrelor; P = Placebo; N = Number of patients

The bleeding events in THEMIS are shown below in Table 6.

Table 6 – Bleeding events (THEMIS)

 | Ticagrelor N=9562 | Placebo N=9531
 | Events / 1000 patient years | Events / 1000 patient years
TIMI Major | 9 | 4
TIMI Major or Minor | 12 | 5
TIMI Major or Minor or Requiring medical attention | 46 | 18
Fatal bleeding | 1 | 0
Intracranial hemorrhage | 3 | 2

Bleeding in THALES (Reduction in risk of stroke in patients with acute ischemic stroke or TIA)

The Kaplan-Meier curve of time course of GUSTO severe bleeding events is presented in Figure 4.

Figure 4 - Time course of GUSTO severe bleeding events

KM%: Kaplan-Meier percentage evaluated at Day 30; T = Ticagrelor; P = placebo; N = Number of patients

GUSTO Severe: Any one of the following: fatal bleeding, intracranial bleeding (excluding asymptomatic hemorrhagic transformations of ischemic brain infarctions and excluding microhemorrhages < 10 mm evident only on gradient-echo magnetic resonance imaging), bleeding that caused hemodynamic compromise requiring intervention (eg, systolic blood pressure <90 mmg Hg that required blood or fluid replacement, or vasopressor/inotropic support, or surgical intervention).

Intracranial bleeding and fatal bleeding in THALES: In total, there were 21 intracranial hemorrhages (ICHs) for ticagrelor and 6 ICHs for placebo. Fatal bleedings, almost all ICH, occurred in 11 for ticagrelor and in 2 for placebo.

Bradycardia

THEMIS and THALES excluded patients at increased risk of bradycardic events (e.g., patients who have sick sinus syndrome, 2nd or 3rd degree AV block, or bradycardic-related syncope and not protected with a pacemaker).

6.2 Postmarketing Experience

The following adverse reactions have been identified during post-approval use of ticagrelor. Because these reactions are reported voluntarily from a population of an unknown size, it is not always possible to reliably estimate their frequency or establish a causal relationship to drug exposure.

Blood and lymphatic system disorders: Thrombotic Thrombocytopenic Purpura (TTP) has been rarely reported with the use of ticagrelor. TTP is a serious condition which can occur after a brief exposure (<2 weeks) and requires prompt treatment.

Immune system disorders: Hypersensitivity reactions including angioedema [see Contraindications (4.3)].

Respiratory Disorders: Central sleep apnea, Cheyne-Stokes respiration

Skin and subcutaneous tissue disorders: Rash

7 DRUG INTERACTIONS

7.1 Strong CYP3A Inhibitors

Strong CYP3A inhibitors substantially increase ticagrelor exposure and so increase the risk of dyspnea, bleeding, and other adverse events. Avoid use of strong inhibitors of CYP3A (e.g., ketoconazole, itraconazole, voriconazole, clarithromycin, nefazodone, ritonavir, saquinavir, nelfinavir, indinavir, atazanavir and telithromycin) [see Clinical Pharmacology (12.3)].

7.2 Strong CYP3A Inducers

Strong CYP3A inducers substantially reduce ticagrelor exposure and so decrease the efficacy of ticagrelor. Avoid use with strong inducers of CYP3A (e.g., rifampin, phenytoin, carbamazepine and phenobarbital) [see Clinical Pharmacology (12.3)].

7.3 Opioids

As with other oral P2Y12 inhibitors, co-administration of opioid agonists delay and reduce the absorption of ticagrelor and its active metabolite presumably because of slowed gastric emptying [see Clinical Pharmacology (12.3)]. Consider the use of a parenteral anti-platelet agent in acute coronary syndrome patients requiring co-administration of morphine or other opioid agonists.

7.4 Simvastatin, Lovastatin, Rosuvastatin

Ticagrelor increases serum concentrations of simvastatin and lovastatin because these drugs are metabolized by CYP3A4. Avoid simvastatin and lovastatin doses greater than 40 mg [see Clinical Pharmacology (12.3)].

Ticagrelor increases serum concentration of rosuvastatin because rosuvastatin is a BCRP substrate [see Clinical Pharmacology (12.3)].

7.5 Digoxin

Ticagrelor inhibits the P-glycoprotein transporter; monitor digoxin levels with initiation of or change in ticagrelor therapy [see Clinical Pharmacology (12.3)].

8 USE IN SPECIFIC POPULATIONS

8.1 Pregnancy

Risk Summary

Available data from case reports with ticagrelor use in pregnant women have not identified a drug-associated risk of major birth defects, miscarriage, or adverse maternal or fetal outcomes. Ticagrelor given to pregnant rats and pregnant rabbits during organogenesis caused structural abnormalities in the offspring at maternal doses about 5 to 7 times the maximum recommended human dose (MRHD) based on body surface area. When ticagrelor was given to rats during late gestation and lactation, pup death and effects on pup growth were seen at approximately 10 times the MRHD (see Data).

The estimated background risk of major birth defects and miscarriage for the indicated population is unknown. All pregnancies have a background risk of birth defect, loss, or other adverse outcomes. In the U.S. general population, the estimated background risk of major birth defects and miscarriage in clinically recognized pregnancies is 2 to 4% and 15 to 20%, respectively.

Data

Animal Data

In reproductive toxicology studies, pregnant rats received ticagrelor during organogenesis at doses from 20 to 300 mg/kg/day. 20 mg/kg/day is approximately the same as the MRHD of 90 mg twice daily for a 60 kg human on a mg/m^2 basis. Adverse outcomes in offspring occurred at doses of 300 mg/kg/day (16.5 times the MRHD on a mg/m2 basis) and included supernumerary liver lobe and ribs, incomplete ossification of sternebrae, displaced articulation of pelvis, and misshapen/misaligned sternebrae. At the mid-dose of 100 mg/kg/day (5.5 times the MRHD on a mg/m^2 basis), delayed development of liver and skeleton was seen. When pregnant rabbits received ticagrelor during organogenesis at doses from 21 to 63 mg/kg/day, fetuses exposed to the highest maternal dose of 63 mg/kg/day (6.8 times the MRHD on a mg/m^2 basis) had delayed gall bladder development and incomplete ossification of the hyoid, pubis and sternebrae occurred.

In a prenatal/postnatal study, pregnant rats received ticagrelor at doses of 10 to 180 mg/kg/day during late gestation and lactation. Pup death and effects on pup growth were observed at 180 mg/kg/day (approximately 10 times the MRHD on a mg/m^2 basis). Relatively minor effects such as delays in pinna unfolding and eye opening occurred at doses of 10 and 60 mg/kg (approximately one-half and 3.2 times the MRHD on a mg/m^2 basis).

8.2 Lactation

Risk Summary

There are no data on the presence of ticagrelor or its metabolites in human milk, the effects on the breastfed infant, or the effects on milk production. Ticagrelor and its metabolites were present in rat milk at higher concentrations than in maternal plasma. When a drug is present in animal milk, it is likely that the drug will be present in human milk. Breastfeeding is not recommended during treatment with ticagrelor.

8.4 Pediatric Use

The safety and effectiveness of ticagrelor have not been established in pediatric patients. Effectiveness was not demonstrated in an adequate and well-controlled study conducted in 101 ticagrelor-treated pediatric patients, aged 2 to <18 for reducing the rate of vaso-occlusive crises in sickle cell disease.

8.5 Geriatric Use

About half of the patients in THEMIS and THALES were ≥65 years of age and at least 15% were ≥75 years of age. No overall differences in safety or effectiveness were observed between elderly and younger patients.

8.6 Hepatic Impairment

Ticagrelor is metabolized by the liver and impaired hepatic function can increase risks for bleeding and other adverse events. Avoid use of ticagrelor in patients with severe hepatic impairment. There is limited experience with ticagrelor in patients with moderate hepatic impairment; consider the risks and benefits of treatment, noting the probable increase in exposure to ticagrelor. No dosage adjustment is needed in patients with mild hepatic impairment [see Warnings and Precautions (5.5) and Clinical Pharmacology (12.3)].

8.7 Renal Impairment

No dosage adjustment is needed in patients with renal impairment [see Clinical Pharmacology (12.3)].

Patients with End-Stage Renal Disease on dialysis

Clinical efficacy and safety studies with ticagrelor did not enroll patients with end-stage renal disease (ESRD) on dialysis. In patients with ESRD maintained on intermittent hemodialysis, no clinically significant difference in concentrations of ticagrelor and its metabolite and platelet inhibition are expected compared to those observed in patients with normal renal function [see Clinical Pharmacology (12.3)]. It is not known whether these concentrations will lead to similar efficacy and safety in patients with ESRD on dialysis as were seen in THEMIS and THALES.

10 OVERDOSAGE

There is currently no known treatment to reverse the effects of ticagrelor, and ticagrelor is not dialyzable. Treatment of overdose should follow local standard medical practice. Bleeding is the expected pharmacologic effect of overdosing. If bleeding occurs, appropriate supportive measures should be taken.

Platelet transfusion did not reverse the antiplatelet effect of ticagrelor in healthy volunteers and is unlikely to be of clinical benefit in patients with bleeding.

Other effects of overdose may include gastrointestinal effects (nausea, vomiting, diarrhea) or ventricular pauses. Monitor the ECG.

11 DESCRIPTION

Ticagrelor tablets contains ticagrelor, a cyclopentyltriazolopyrimidine, inhibitor of platelet activation and aggregation mediated by the P2Y12 ADP-receptor. Chemically it is (1S,2S,3R,5S)-3-[7-[[(1R,2S)-2-(3,4-difluorophenyl)cyclopropyl]amino]-5-(propylsulfanyl)-3H-[1,2,3] triazolo[4,5-d]-pyrimidin-3-yl]-5-(2-hydroxyethoxy)cyclopentane-1,2-diol The molecular formula of ticagrelor is C23H28F2N6O4S and its molecular weight is 522.6. The chemical structure of ticagrelor is:

Ticagrelor is off white to pale pink powder with an aqueous solubility of approximately 10 mcg/mL at room temperature. It is freely soluble in dimethylsulphoxide, sparingly soluble in methanol, and insoluble in water.

Ticagrelor tablets for oral administration contain 60 mg or 90 mg of ticagrelor and the following ingredients: croscarmellose sodium, dicalcium phosphate dihydrate, hypromellose, magnesium stearate, mannitol, polyethylene glycol, povidone, and titanium dioxide. The 60 mg tablets also contain D&C yellow #10 aluminum lake, FD&C blue #1 aluminum lake, and FD&C red #40 aluminum lake. The 90 mg tablets also contain talc.

12 CLINICAL PHARMACOLOGY

12.1 Mechanism of Action

Ticagrelor and its major metabolite reversibly interact with the platelet P2Y12 ADP-receptor to prevent signal transduction and platelet activation. Ticagrelor and its active metabolite are approximately equipotent.

12.2 Pharmacodynamics

The inhibition of platelet aggregation (IPA) by ticagrelor and clopidogrel was compared in a 6-week study examining both acute and chronic platelet inhibition effects in response to 20 μM ADP as the platelet aggregation agonist.

The onset of IPA was evaluated on Day 1 of the study following loading doses of 180 mg ticagrelor or 600 mg clopidogrel. As shown in Figure 5, IPA was higher in the ticagrelor group at all time points. The maximum IPA effect of ticagrelor was reached at around 2 hours, and was maintained for at least 8 hours.

The offset of IPA was examined after 6 weeks on ticagrelor 90 mg twice daily or clopidogrel 75 mg daily, again in response to 20 μM ADP.

As shown in Figure 6, mean maximum IPA following the last dose of ticagrelor was 88% and 62% for clopidogrel. The insert in Figure 6 shows that after 24 hours, IPA in the ticagrelor group (58%) was similar to IPA in clopidogrel group (52%), indicating that patients who miss a dose of ticagrelor would still maintain IPA similar to the trough IPA of patients treated with clopidogrel. After 5 days, IPA in the ticagrelor group was similar to IPA in the placebo group. It is not known how either bleeding risk or thrombotic risk track with IPA, for either ticagrelor or clopidogrel.

Figure 5 – Mean inhibition of platelet aggregation (±SE) following single oral doses of placebo, 180 mg ticagrelor or 600 mg clopidogrel

Figure 6 - Mean inhibition of platelet aggregation (IPA) following 6 weeks on placebo, ticagrelor 90 mg twice daily, or clopidogrel 75 mg daily

Transitioning from clopidogrel to ticagrelor resulted in an absolute IPA increase of 26.4% and from ticagrelor to clopidogrel resulted in an absolute IPA decrease of 24.5%. Patients can be transitioned from clopidogrel to ticagrelor without interruption of antiplatelet effect [see Dosage and Administration (2)].

12.3 Pharmacokinetics

Ticagrelor demonstrates dose proportional pharmacokinetics, which are similar in patients and healthy volunteers.

Absorption

Ticagrelor can be taken with or without food. Absorption of ticagrelor occurs with a median tmax of 1.5 h (range 1.0–4.0). The formation of the major circulating metabolite AR-C124910XX (active) from ticagrelor occurs with a median tmax of 2.5 h (range 1.5-5.0).

The mean absolute bioavailability of ticagrelor is about 36% (range 30%-42%). Ingestion of a high-fat meal had no effect on ticagrelor Cmax, but resulted in a 21% increase in AUC. The Cmax of its major metabolite was decreased by 22% with no change in AUC.

Ticagrelor as crushed tablets mixed in water, given orally or administered through a nasogastric tube into the stomach, is bioequivalent to whole tablets (AUC and Cmax within 80-125% for ticagrelor and AR-C124910XX) with a median tmax of 1.0 hour (range 1.0 – 4.0) for ticagrelor and 2.0 hours (range 1.0 –8.0) for AR-C124910XX.

Distribution

The steady state volume of distribution of ticagrelor is 88 L. Ticagrelor and the active metabolite are extensively bound to human plasma proteins (>99%).

Metabolism

CYP3A4 is the major enzyme responsible for ticagrelor metabolism and the formation of its major active metabolite. Ticagrelor and its major active metabolite are weak P-glycoprotein substrates and inhibitors. The systemic exposure to the active metabolite is approximately 30-40% of the exposure of ticagrelor. Ticagrelor is a BCRP inhibitor.

Excretion

The primary route of ticagrelor elimination is hepatic metabolism. When radiolabeled ticagrelor is administered, the mean recovery of radioactivity is approximately 84% (58% in feces, 26% in urine). Recoveries of ticagrelor and the active metabolite in urine were both less than 1% of the dose. The primary route of elimination for the major metabolite of ticagrelor is most likely to be biliary secretion. The mean t1/2 is approximately 7 hours for ticagrelor and 9 hours for the active metabolite.

Specific Populations

The effects of age, gender, ethnicity, renal impairment and mild hepatic impairment on the pharmacokinetics of ticagrelor are presented in Figure 7. Effects are modest and do not require dose adjustment.

Patients with End-Stage Renal Disease on Hemodialysis

In patients with end stage renal disease on hemodialysis AUC and Cmax of ticagrelor 90 mg administered on a day without dialysis were 38% and 51% higher respectively, compared to subjects with normal renal function. A similar increase in exposure was observed when ticagrelor was administered immediately prior to dialysis showing that ticagrelor is not dialyzable. Exposure of the active metabolite increased to a lesser extent. The IPA effect of ticagrelor was independent of dialysis in patients with end stage renal disease and similar to healthy adults with normal renal function.

Figure 7 – Impact of intrinsic factors on the pharmacokinetics of ticagrelor

* Single-dose of ticagrelor administered on a day without dialysis

** Ticagrelor has not been studied in patients with moderate or severe hepatic impairment

Effects of Other Drugs on Ticagrelor

CYP3A4 is the major enzyme responsible for ticagrelor metabolism and the formation of its major active metabolite. The effects of other drugs on the pharmacokinetics of ticagrelor are presented in Figure 8 as change relative to ticagrelor given alone (test/reference). Strong CYP3A inhibitors (e.g., ketoconazole, itraconazole, and clarithromycin) substantially increase ticagrelor exposure. Moderate CYP3A inhibitors have lesser effects (e.g., diltiazem). CYP3A inducers (e.g., rifampin) substantially reduce ticagrelor blood levels. P-gp inhibitors (e.g., cyclosporine) increase ticagrelor exposure.

Co-administration of 5 mg intravenous morphine with 180 mg loading dose of ticagrelor decreased observed mean ticagrelor exposure by up to 25% in healthy adults and up to 36% in ACS patients undergoing PCI. Tmax was delayed by 1-2 hours. Exposure of the active metabolite decreased to a similar extent. Morphine co-administration did not delay or decrease platelet inhibition in healthy adults. Mean platelet aggregation was higher up to 3 hours post loading dose in ACS patients co-administered with morphine.

Co-administration of intravenous fentanyl with 180 mg loading dose of ticagrelor in ACS patients undergoing PCI resulted in similar effects on ticagrelor exposure and platelet inhibition.

Figure 8 – Effect of co-administered drugs on the pharmacokinetics of ticagrelor

*See Dosage and Administration (2)

Effects of Ticagrelor on Other Drugs

In vitro metabolism studies demonstrate that ticagrelor and its major active metabolite are weak inhibitors of CYP3A4, potential activators of CYP3A5 and inhibitors of the P-gp transporter. In vitro metabolism studies demonstrate that ticagrelor is a BCRP inhibitor. Ticagrelor and AR-C124910XX were shown to have no inhibitory effect on human CYP1A2, CYP2C19, and CYP2E1 activity. For specific in vivo effects on the pharmacokinetics of simvastatin, atorvastatin, ethinyl estradiol, levonorgesterol, tolbutamide, digoxin and cyclosporine, see Figure 9.

Figure 9 – Impact of Ticagrelor on the pharmacokinetics of co-administered drugs

* Similar increases in AUC and Cmax were observed for all metabolites

** Monitor digoxin levels with initiation of or change in ticagrelor therapy

13 NONCLINICAL TOXICOLOGY

13.1 Carcinogenesis, Mutagenesis, Impairment of Fertility

Carcinogenesis

Ticagrelor was not carcinogenic in the mouse at doses up to 250 mg/kg/day or in the male rat at doses up to 120 mg/kg/day (19 and 15 times the MRHD of 90 mg twice daily on the basis of AUC, respectively). Uterine carcinomas, uterine adenocarcinomas and hepatocellular adenomas were seen in female rats at doses of 180 mg/kg/day (29-fold the maximally recommended dose of 90 mg twice daily on the basis of AUC), whereas 60 mg/kg/day (8-fold the MRHD based on AUC) was not carcinogenic in female rats.

Mutagenesis

Ticagrelor did not demonstrate genotoxicity when tested in the Ames bacterial mutagenicity test, mouse lymphoma assay and the rat micronucleus test. The active O-demethylated metabolite did not demonstrate genotoxicity in the Ames assay and mouse lymphoma assay.

Impairment of Fertility

Ticagrelor had no effect on male fertility at doses up to 180 mg/kg/day or on female fertility at doses up to 200 mg/kg/day (>15-fold the MRHD on the basis of AUC). Doses of ≥10 mg/kg/day given to female rats caused an increased incidence of irregular duration estrus cycles (1.5-fold the MRHD based on AUC).

14 CLINICAL STUDIES

14.2 Coronary Artery Disease but No Prior Stroke or Myocardial Infarction

THEMIS

The THEMIS study (NCT01991795) was a double-blind, parallel group, study in which 19,220 patients with CAD and Type 2 Diabetes Mellitus (T2DM) but no history of MI or stroke were randomized to twice daily ticagrelor or placebo, on a background of 75-150 mg of aspirin. The primary endpoint was the composite of first occurrence of CV death, MI, and stroke. CV death, MI, ischemic stroke, and all-cause death were assessed as secondary endpoints.

Patients were eligible to participate if they were ≥ 50 years old with CAD, defined as a history of PCI or CABG, or angiographic evidence of ≥ 50% lumen stenosis of at least 1 coronary artery and T2DM treated for at least 6 months with glucose-lowering medication. Patients with previous intracerebral hemorrhage, gastrointestinal bleeding within the past 6 months, known bleeding diathesis, and coagulation disorder were excluded. Patients taking anticoagulants or ADP receptor antagonists were excluded from participating, and patients who developed an indication for those medications during the trial were discontinued from study drug.

Patients were treated for a median of 33 months and up to 58 months.

Patients were predominantly male (69%) with a mean age of 66 years. At baseline, 80% had a history of coronary artery revascularization; 58% had undergone PCI, 29% had undergone a CABG and 7% had undergone both. The proportion of patients studied in the US was 12%. Patients in THEMIS had established CAD and other risk factors that put them at higher cardiovascular risk.

Ticagrelor was superior to placebo in reducing the incidence of CV death, MI, or stroke. The effect on the composite endpoint was driven by the individual components MI and stroke; see Table 9.

Table 9 – Primary composite endpoint, primary endpoint components, and secondary endpoints (THEMIS)

 | Ticagrelor N=9619 | Placebo N=9601 | HR (95% CI) | p -value
 | Events / 1000 patient years | Events / 1000 patient years | HR (95% CI) | p -value
Time to first CV death, MI, or stroke* | 24 | 27 | 0.90 (0.81, 0.99) | 0.04
CV death† | 12 | 11 | 1.02 (0.88, 1.18)
Myocardial infarction† | 9 | 11 | 0.84 (0.71, 0.98)
Stroke† | 6 | 7 | 0.82 (0.67, 0.99)
Secondary endpoints
CV death | 12 | 11 | 1.02 (0.88, 1.18)
Myocardial infarction | 9 | 11 | 0.84 (0.71, 0.98)
Ischemic stroke | 5 | 6 | 0.80 (0.64, 0.99)
All-cause death | 18 | 19 | 0.98 (0.87, 1.10)

CI = Confidence interval; CV = Cardiovascular; HR = Hazard ratio; MI = Myocardial infarction.

* Primary endpoint

† The event rate for the components CV death, MI and stroke are calculated from the actual number of first events for each component.

The Kaplan-Meier curve (Figure 15) shows time to first occurrence of the primary composite endpoint of CV death, MI, or stroke.

Figure 15 - Time to First Occurrence of CV death, MI or Stroke (THEMIS)

T = Ticagrelor; P = Placebo; N = Number of patients.

The treatment effect of ticagrelor appeared similar across patient subgroups, see Figure 16.

Figure 16 –Subgroup analyses of ticagrelor (THEMIS)

Note: The figure above presents effects in various subgroups all of which are baseline characteristics. The 95% confidence limits that are shown do not take into account how many comparisons were made, nor do they reflect the effect of a particular factor after adjustment for all other factors. Apparent homogeneity or heterogeneity among groups should not be over-interpreted.

14.3 Acute Ischemic Stroke or Transient Ischemic Attack (TIA)

THALES

The THALES study (NCT03354429) was a 11,016-patient, randomized, double-blind, parallel-group study of ticagrelor 90 mg twice daily versus placebo in patients with acute ischemic stroke or transient ischemic attack (TIA). The primary endpoint was the first occurrence of the composite of stroke and death up to 30 days. Ischemic stroke was assessed as one of the secondary endpoints.

Patients were eligible to participate if they were ≥40 years old, with non-cardioembolic acute ischemic stroke (NIHSS score ≤5) or high-risk TIA (defined as ABCD2 score ≥6 or ipsilateral atherosclerotic stenosis ≥50% in the internal carotid or an intracranial artery). Patients who received thrombolysis or thrombectomy within 24 hours prior to randomization were not eligible.

Patients were randomized within 24 hours of onset of an acute ischemic stroke or TIA to receive 30 days of either ticagrelor (90 mg twice daily, with an initial loading dose of 180 mg) or placebo, on a background of aspirin initially 300-325 mg then 75-100 mg daily. The median treatment duration was 31 days.

Ticagrelor was superior to placebo in reducing the rate of the primary endpoint (composite of stroke and death), corresponding to a relative risk reduction (RRR) of 17% and an absolute risk reduction (ARR) of 1.1% (Table 10). The effect was driven primarily by a significant reduction in the stroke component of the primary endpoint (19% RRR, 1.1% ARR).

Table 10 - Incidences of the primary composite endpoint, primary composite endpoint components, and secondary endpoint (THALES)

 | Ticagrelor N=5523 |  | Placebo N=5493 |  | HR (95% CI) | p -value
 | n (patients with event) | KM% | n (patients with event) | KM% | HR (95% CI) | p -value
Time to first Stroke or Death | 303 | 5.4% | 362 | 6.5% | 0.83 (0.71, 0.96) | 0.015
Time to first Stroke* | 284 | 5.1% | 347 | 6.3% | 0.81 (0.69, 0.95)
Time to Death* | 36 | 0.6% | 27 | 0.5% | 1.33 (0.81, 2.19)
Secondary Endpoint
Time to first Ischemic Stroke | 276 | 5.0% | 345 | 6.2% | 0.79 (0.68, 0.93) | 0.004

CI = Confidence interval; HR = Hazard ratio; KM = Kaplan-Meier percentage calculated at 30 days; N = Number of patients

*The number of patients with the event of interest. In the time to first stroke, patients who died are censored at the time of death.

The Kaplan-Meier curve (Figure 17) shows the time to first occurrence of the primary composite endpoint of stroke and death.

Figure 17 – Time to First Occurrence of Stroke or Death (THALES)

KM%: Kaplan-Meier percentage evaluated at Day 30; T=Ticagrelor; P=placebo; N=Number of patients

Ticagrelor's treatment effect on stroke and on death accrued over the first 10 days and was sustained at 30 days. Although not studied, this suggests that shorter treatment could result in similar benefit and reduced bleeding risk.

The treatment effect of ticagrelor was generally consistent across pre-defined subgroups (Figure 18).

Figure 18 – Subgroup analyses of ticagrelor 90 mg (THALES)

Note: The figure above presents effects in various subgroups all of which are baseline characteristics and were pre-specified. The 95% confidence limits that are shown do not take into account how many comparisons were made, nor do they reflect the effect of a particular factor after adjustment for all other factors. Apparent homogeneity or heterogeneity among groups should not be over-interpreted.

At Day 30, there was an absolute reduction of 1.2% (95% CI: -2.1%, -0.3%) in the incidence of non-hemorrhagic stroke and death (excluding fatal bleed) favoring ticagrelor (294 events: 5.3%) over placebo (359 events: 6.5%) in the intention-to-treat population. In the same population, there was an absolute increase of 0.4% (95% CI: 0.2%, 0.6%) in the incidence of GUSTO severe bleeding unfavorable to ticagrelor arm (28 events: 0.5%) compared to the placebo arm (7 events: 0.1%).

16 HOW SUPPLIED/STORAGE AND HANDLING

Ticagrelor tablets 60 mg are supplied as light green to green colored, round, biconvex, film-coated tablets, debossed with 'L47' on one side and plain on other side.

Bottles of 60's with a child-resistant closure NDC 70756-047-60

Ticagrelor tablets 90 mg are supplied as white to off white, round, biconvex, film-coated tablets, debossed with 'L48' on one side and plain on other side.

Bottles of 60's with a child-resistant closure NDC 70756-048-60

Carton of 100 (10 x 10 Unit-dose Tablets) child-resistant NDC 70756-048-99

Storage and Handling

Store at 20° to 25°C (68° to 77°F); excursions permitted to 15° to 30°C (59° to 86°F) [see USP Controlled Room Temperature].

17 PATIENT COUNSELING INFORMATION

Advise the patient to read the FDA-approved patient labeling (Medication Guide).

Advise patients daily doses of aspirin should not exceed 100 mg and to avoid taking any other medications that contain aspirin.

Advise patients that they:

- Will bleed and bruise more easily
- Will take longer than usual to stop bleeding
- Should report any unanticipated, prolonged or excessive bleeding, or blood in their stool or urine.

Advise patients to contact their doctor if they experience unexpected shortness of breath, especially if severe.

Advise patients to inform physicians and dentists that they are taking ticagrelor before any surgery or dental procedure.

Advise women that breastfeeding is not recommended during treatment with ticagrelor [see Use in Specific Populations (8.2)].

Manufactured for:

Lifestar Pharma LLC

1200 MacArthur Blvd.

Mahwah, NJ 07430 USA

Made in India

Revised: January 2026, V-08

SPL MEDGUIDE

MEDICATION GUIDE
Ticagrelor Tablets
(tye ka' grel or)

<br/> What is the most important information I should know about ticagrelor tablets?
<br/> Ticagrelor tablets are used to lower your chance of having, or dying from, a heart attack or stroke. Ticagrelor tablets (and similar drugs) can cause bleeding that can be serious and sometimes lead to death. In cases of serious bleeding, such as internal bleeding, the bleeding may result in the need for blood transfusions or surgery. While you take ticagrelor tablets:

- you may bruise and bleed more easily
- you are more likely to have nose bleeds
- it will take longer than usual for any bleeding to stop

<br/>Call your healthcare provider right away, if you have any of these signs or symptoms of bleeding while taking ticagrelor tablets:

- bleeding that is severe or that you cannot control
- pink, red or brown urine
- vomiting blood or your vomit looks like "coffee grounds"
- red or black stools (looks like tar)
- coughing up blood or blood clots

<br/>Do not stop taking ticagrelor tablets without talking to the healthcare provider who prescribes it for you. People who are treated with a stent, and stop taking ticagrelor tablets too soon, have a higher risk of getting a blood clot in the stent, having a heart attack, or dying. If you stop ticagrelor tablets because of bleeding, or for other reasons, your risk of a heart attack or stroke may increase.
<br/> Your healthcare provider may instruct you to stop taking ticagrelor tablets 5 days before surgery. This will help to decrease your risk of bleeding with your surgery or procedure. Your healthcare provider should tell you when to start taking ticagrelor tablets again, as soon as possible after surgery.
<br/> Taking ticagrelor tablets with aspirin
<br/>Ticagrelor tablets are taken with aspirin, unless your healthcare provider specifically tells you otherwise. Talk to your healthcare provider about the dose of aspirin that you should take with ticagrelor tablets. In most cases, you should not take a dose of aspirin higher than 100 mg daily. Do not take doses of aspirin higher than what your healthcare provider tells you to take. Tell your healthcare provider if you take other medicines that contain aspirin, and do not take new over-the-counter medicines with aspirin in them.

<br/>What are ticagrelor tablets?
<br/>Ticagrelor tablets are prescription medicine used to:

- decrease your risk of a first heart attack or stroke in people who have a condition where the blood flow to the heart is decreased (coronary artery disease or CAD) who are at high risk for having a heart attack or stroke.
- decrease your risk of stroke in people who are having a stroke (acute ischemic stroke) or mini-stroke (transient ischemic attack or TIA).

<br/> It is not known if ticagrelor tablets are safe and effective in children.

<br/> Do not take ticagrelor tablets if you:

- have a history of bleeding in the brain
- are bleeding now
- are allergic to ticagrelor or any of the ingredients in ticagrelor tablets. See the end of this Medication Guide for a complete list of ingredients in ticagrelor tablets.

<br/>Before taking ticagrelor tablets, tell your healthcare provider about all of your medical conditions, if you:

- have had bleeding problems in the past
- have had any recent serious injury or surgery
- plan to have surgery or a dental procedure. See "What is the most important information I should know about ticagrelor tablets?
- have a history of stomach ulcers or colon polyps
- have lung or breathing problems, such as COPD or asthma
- have liver problems
- have a history of stroke
- are pregnant or plan to become pregnant. It is not known if ticagrelor tablets will harm your unborn baby. You and your healthcare provider should decide if you will take ticagrelor tablets.
- are breastfeeding or plan to breastfeed. It is not known if ticagrelor passes into your breast milk. You should not breastfeed during treatment with ticagrelor tablets. Talk to your healthcare provider about the best way to feed your baby during treatment with ticagrelor tablets.

<br/> Tell all of your healthcare providers and dentists that you are taking ticagrelor tablets. They should talk to the healthcare provider who prescribed ticagrelor tablets for you before you have any surgery or procedure.
<br/>Tell your healthcare providers about all the medicines you take, including prescription and over-the-counter medicines, vitamins, and herbal supplements. Ticagrelor tablets may affect the way other medicines work, and other medicines may affect how ticagrelor tablet works. Certain medicines may increase your risk of bleeding.
<br/> Know the medicines you take. Keep a list of them to show your healthcare provider and pharmacist when you get a new medicine.

<br/>How should I take ticagrelor tablets?

- Take ticagrelor tablets exactly as prescribed by your healthcare provider.
- Your healthcare provider will tell you how many ticagrelor tablets to take and when to take them.
- Take ticagrelor tablets with aspirin, unless your healthcare provider specifically tells you otherwise. See "What is the most important information I should know about ticagrelor tablets?".
- You may take ticagrelor tablets with or without food.
- Take ticagrelor tablets two times each day, around the same times each day.
- If you miss your scheduled dose of ticagrelor tablets, take your next dose at its scheduled time. Do not take 2 doses at the same time unless your healthcare provider tells you to.
- If you take too much ticagrelor tablets, call your healthcare provider or local poison control center or go to the nearest emergency room right away
- If you are unable to swallow the tablet(s) whole, you may crush the ticagrelor tablet(s) and mix it with water. Drink all the water right away. Refill the glass with water, stir, and drink all the water.
- Ticagrelor tablets may also be given through certain nasogastric (NG) tubes. Ask your healthcare provider for instructions on how to take ticagrelor tablets through a NG tube."

<br/>What are the possible side effects of ticagrelor tablets?
<br/> Ticagrelor tablets can cause serious side effects, including:

- See "What is the most important information I should know about ticagrelor tablets?"
- Shortness of breath. Tell your healthcare provider if you have new worsening or unexpected shortness of breath when you are at rest, at night, or when you are doing any activity.

Slow or irregular heartbeat

- Irregular breathing. Tell your healthcare provider if you develop irregular breathing patterns when asleep or awake such as speeding up, slowing down or short pauses in breathing. Your healthcare provider will decide if you need further evaluation.

<br/> These are not all of the possible side effects of ticagrelor tablets.
<br/> Call your doctor for medical advice about side effects. You may report side effects to FDA at 1-800-FDA-1088.

<br/> How should I store ticagrelor tablets?

- Store ticagrelor tablets at room temperature between 68°F to 77°F (20°C to 25°C).
- Ticagrelor tablets comes in a child-resistant package

<br/> Keep ticagrelor tablets and all medicines out of the reach of children.

<br/> General information about the safe and effective use of ticagrelor tablets.
<br/> Medicines are sometimes prescribed for purposes other than those listed in a Medication Guide. Do not use ticagrelor tablets for a condition for which it was not prescribed. Do not give ticagrelor tablets to other people, even if they have the same symptoms you have. It may harm them. You can ask your pharmacist or healthcare provider for information about ticagrelor tablets that is written for health professionals.

<br/> What are the ingredients in ticagrelor tablets?
<br/> Active ingredient: ticagrelor.
<br/> Inactive ingredients: croscarmellose sodium, dicalcium phosphate dihydrate, hypromellose, magnesium stearate, mannitol, polyethylene glycol, povidone, and titanium dioxide. The 60 mg tablets also contain D&C yellow #10 aluminum lake, FD&C blue #1 aluminum lake, and FD&C red #40 aluminum lake. The 90 mg tablets also contain talc.
<br/> For more information, call Lifestar Pharma LLC at 1-888-995-4337.
<br/> Manufactured for:
Lifestar Pharma LLC
1200 MacArthur Blvd.
Mahwah, NJ 07430 USA
<br/> Made in India
<br/> This Medication Guide has been approved by the U.S. Food and Drug Administration.
<br/> Revised: January 2026, V-05

PACKAGE LABEL.PRINCIPAL DISPLAY PANEL

60 mg Bottle Label

NDC 70756-047-60

Ticagrelor Tablets

60 mg

PHARMACIST: Dispense the Medication Guide provided separately to each patient

Rx only

60 tablets

PACKAGE LABEL.PRINCIPAL DISPLAY PANEL

90 mg Bottle Label

NDC 70756-048-60

Ticagrelor Tablets

90 mg

PHARMACIST: Dispense the Medication Guide provided separately to each patient

Rx only

60 tablets

90 mg Unit-dose Blister Pack

NDC 70756-048-99

Ticagrelor Tablets

90 mg

PHARMACIST: Dispense the Medication Guide provided separately to each patient.

100 (10 x 10) Unit-dose Tablets

Rx only

90 mg Blister Foil